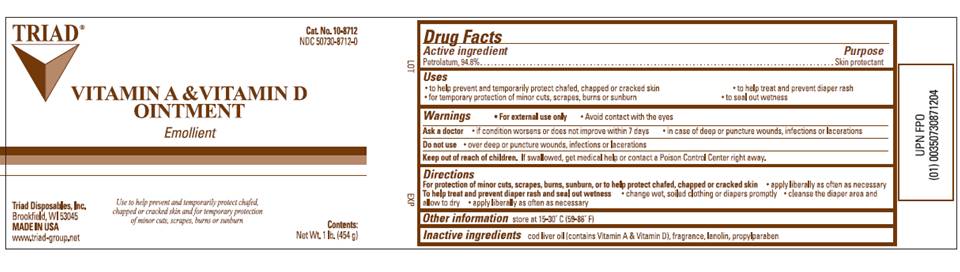 DRUG LABEL: Vitamin A and D
NDC: 50730-8712 | Form: OINTMENT
Manufacturer: H and P Industries, Inc. dba Triad Group
Category: otc | Type: HUMAN OTC DRUG LABEL
Date: 20091119

ACTIVE INGREDIENTS: Petrolatum .948 g/1 g
INACTIVE INGREDIENTS: Cod liver oil; Lanolin; Propylparaben

DRUG FACTS

ACTIVE INGREDIENT

Petrolatum, 94.8%

PURPOSE

skin protectant

USES

- to help prevent and temporarily protect chafed, chapped or cracked skin
- for temporary protection of minor cuts, scrapes, burns or sunburn
- to help treat and prevent diaper rash
- to seal out wetness

WARNINGS

- For external use only

- Avoid contact with the eyes

DO NOT USE

over deep or puncture wounds, infections or lacerations

ASK A DOCTOR BEFORE USE

- if condition worsens or does not improve within 7 days
- in case of deep or puncture wounds, infections or lacerations

KEEP OUT OF REACH OF CHILDREN

If swallowed, get medical help or contact a Poison Control Center right away.

DIRECTIONS

For protection of minor cuts, scrapes, burns, sunburn, or to help protect chafed, chapped or cracked skin

- apply liberally as often as necessary

To help treat and prevent diaper rash and seal out wetness

- change wet soiled clothing or diapers promptly
- cleanse the diaper area and allow to dry
- apply liberally as often as necessary

OTHER INFORMATION

Store at 15°- 30° C (59° - 86° F)

INACTIVE INGREDIENTS

cod liver oil (contains Vitamin A and Vitamin D), fragrance, lanolin, propylparaben

PACKAGE INFORMATION

TRIAD
Cat. No.10-8712
NDC 50730-8712-0
VITAMIN A AND VITAMIN D
OINTMENT
Emollient
Use to help prevent and temporarily protect chafed, chapped or cracked skin and for temporary protection of minor cuts, scrapes, burns or sunburn
CONTENTS:
Net Wt. 1lb. (454 g)
Triad Disposables, Inc.
Brookfield, WI 53045
MADE IN USA
www.triad-group.net